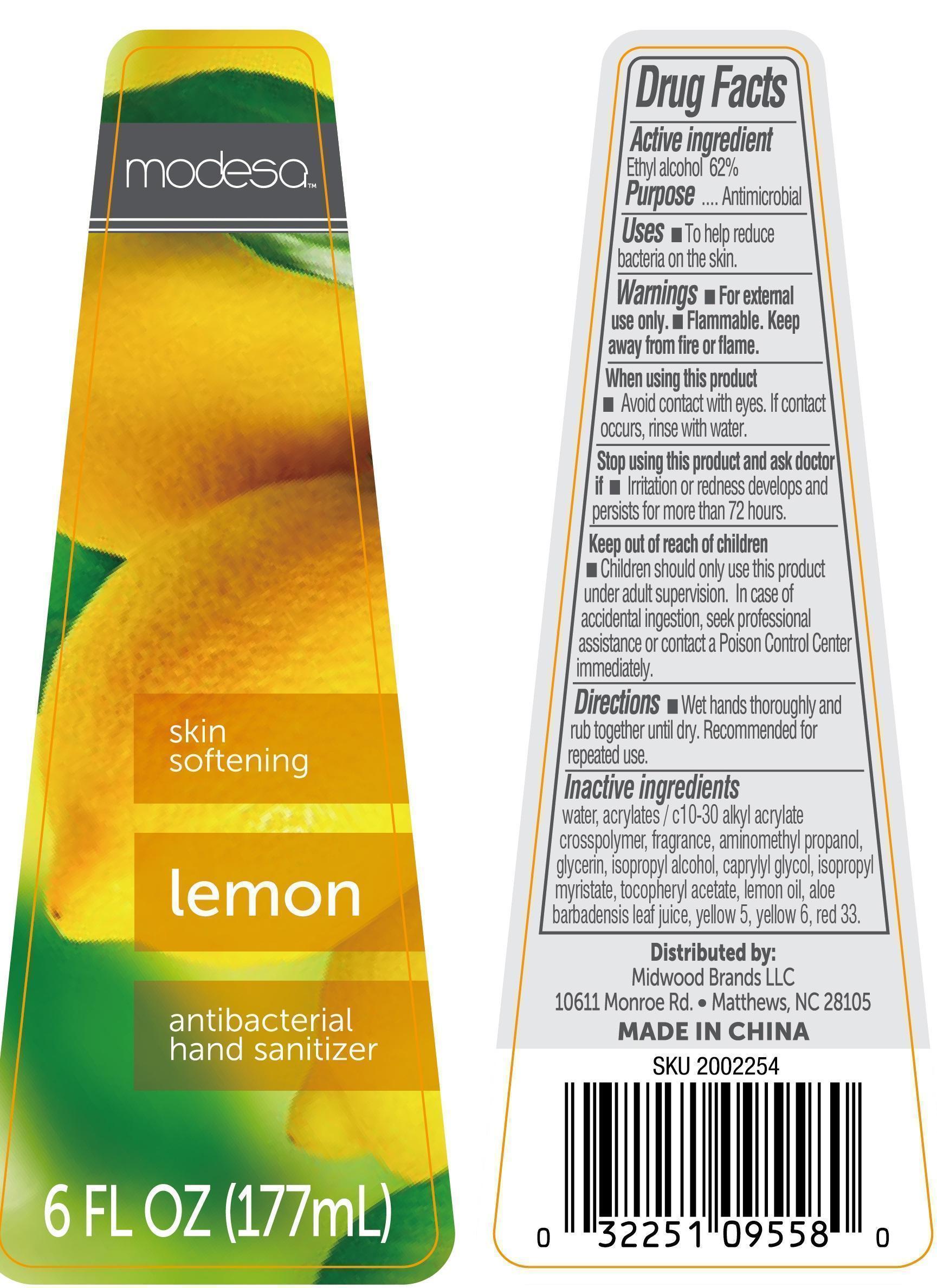 DRUG LABEL: modesa antibacterial hand sanitizer lemon
NDC: 40104-139 | Form: GEL
Manufacturer: Ningbo Pulisi Daily Chemical Products Co., Ltd.
Category: otc | Type: HUMAN OTC DRUG LABEL
Date: 20141216

ACTIVE INGREDIENTS: alcohol 62 mL/100 mL
INACTIVE INGREDIENTS: WATER; PROPYLENE GLYCOL; ALOE VERA LEAF; CARBOMER 934; GLYCERIN; .ALPHA.-TOCOPHEROL ACETATE, D-; FD&C YELLOW NO. 5

Drug facts

Active ingredient Purpose

Alcohol 62% ... Antimicrobial

PURPOSE

to help reduce bacteria on the skin

KEEP OUT OF REACH OF CHILDREN

Children should only use this product under adult supervison. In case of accidental ingstion, seek proessional assistance or contact a Poson Control Center immediately.

INDICATIONS AND USAGE

Avoid contact with eyes. If contact occurs, rinse with water.

WARNINGS

For external use only.
Flammable. Keep away from hear or flame.
Stop using and ask a doctor, if irritation and redness develops and persists for more than 72 hours.

DOSAGE AND ADMINISTRATION

Wet hands thoroughly and rub together until dry. Recommended for repeated use.

INACTIVE INGREDIENT

Water, Carbomer, Glycerin, Propylene Glycol, Triethanolamine, Aloe Barbadensis Leaf Juice, Tocopheryl Acetate, Fragrance